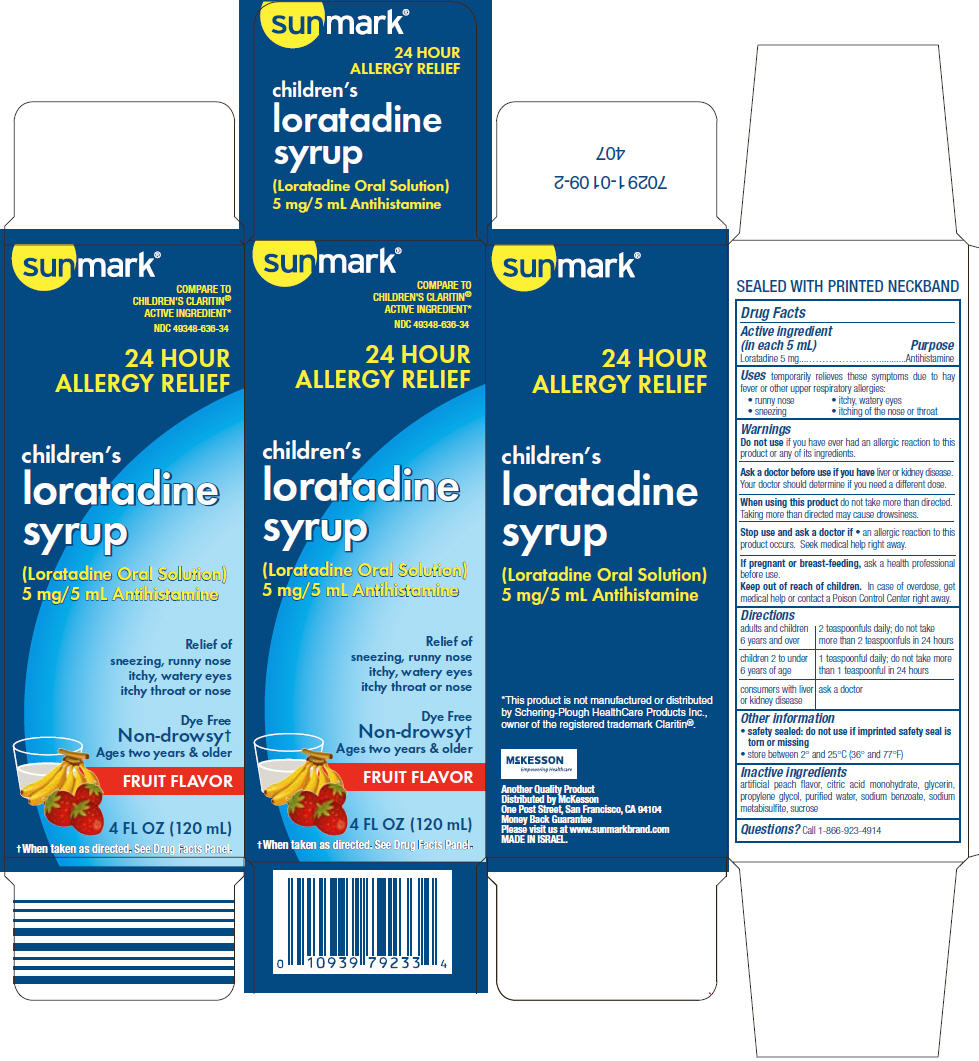 DRUG LABEL: Sunmark 

NDC: 49348-636 | Form: SOLUTION
Manufacturer: Strategic Sourcing Services LLC
Category: otc | Type: HUMAN OTC DRUG LABEL
Date: 20241219

ACTIVE INGREDIENTS: LORATADINE 5 mg/5 mL
INACTIVE INGREDIENTS: CITRIC ACID MONOHYDRATE; GLYCERIN; PROPYLENE GLYCOL; WATER; SODIUM BENZOATE; SODIUM METABISULFITE; SUCROSE

Sunmark®
children's loratadine syrup

Drug Facts

Active ingredient (in each 5 mL)

Loratadine 5 mg

Purpose

Antihistamine

Uses

temporarily relieves these symptoms due to hay fever or other upper respiratory allergies:

- runny nose
- itchy, watery eyes
- sneezing
- itching of the nose or throat

Warnings

DO NOT USE

Do not useif you have ever had an allergic reaction to this product or any of its ingredients.

Ask a doctor before use if you haveliver or kidney disease. Your doctor should determine if you need a different dose.

WHEN USING

When using this productdo not take more than directed. Taking more than directed may cause drowsiness.

Stop use and ask a doctor if

- an allergic reaction to this product occurs. Seek medical help right away.

PREGNANCY OR BREAST FEEDING

If pregnant or breast-feeding,ask a health professional before use.

Keep out of reach of children.In case of overdose, get medical help or contact a Poison Control Center right away.

Directions

adults and children 6 years and over | 2 teaspoonfuls daily; do not take more than 2 teaspoonfuls in 24 hours
children 2 to under 6 years of age | 1 teaspoonful daily; do not take more than 1 teaspoonful in 24 hours
consumers with liver or kidney disease | ask a doctor

Other information

- safety sealed: do not use if imprinted safety seal is torn or missing
- store between 2° and 25°C (36° and 77°F)

Inactive ingredients

artificial peach flavor, citric acid monohydrate, glycerin, propylene glycol, purified water, sodium benzoate, sodium metabisulfite, sucrose

Questions?

Call 1-866-923-4914

Distributed by McKesson
One Post Street, San Francisco, CA 94104

PRINCIPAL DISPLAY PANEL - 120 mL Bottle Carton

sunmark®

COMPARE TO
CHILDREN'S CLARITIN®
ACTIVE INGREDIENT*

NDC 49348-636-34

24 HOUR
ALLERGY RELIEF

children's
loratadine
syrup

(Loratadine Oral Solution)
5 mg/5 mL Antihistamine

Relief of
sneezing, runny nose
itchy, watery eyes
itchy throat or nose

Dye Free
Non-drowsy†
Ages two years & older

FRUIT FLAVOR

4 FL OZ (120 mL)

†When taken as directed. See Drug Facts Panel.